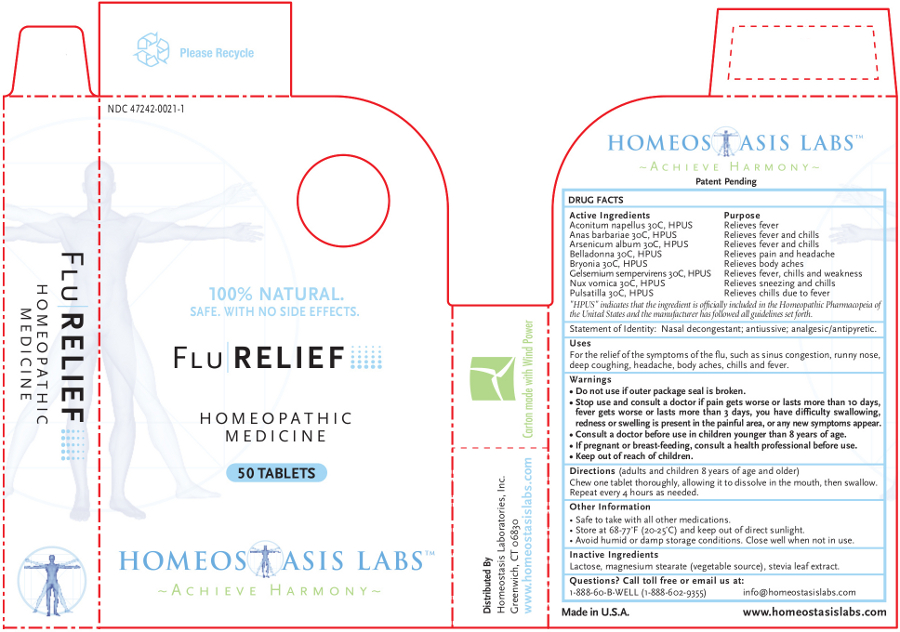 DRUG LABEL: Flu RELIEF
NDC: 47242-0021 | Form: TABLET, CHEWABLE
Manufacturer: Homeostasis Laboratories, Inc.
Category: homeopathic | Type: HUMAN OTC DRUG LABEL
Date: 20121114

ACTIVE INGREDIENTS: ACONITUM NAPELLUS 30 [hp_C]/1 1; CAIRINA MOSCHATA HEART/LIVER AUTOLYSATE 30 [hp_C]/1 1; ARSENIC TRIOXIDE 30 [hp_C]/1 1; BRYONIA ALBA ROOT 30 [hp_C]/1 1; GELSEMIUM SEMPERVIRENS ROOT 30 [hp_C]/1 1; STRYCHNOS NUX-VOMICA SEED 30 [hp_C]/1 1; PULSATILLA VULGARIS 30 [hp_C]/1 1
INACTIVE INGREDIENTS: LACTOSE; MAGNESIUM STEARATE; STEVIA REBAUDIUNA LEAF

Flu RELIEF

Active Ingredients | Purpose
Aconitum napellus 30C, HPUS | Relieves fever
Anas barbariae 30C, HPUS | Relieves fever and chills
Arsenicum album 30C, HPUS | Relieves fever and chills
Belladonna 30C, HPUS | Relieves pain and headache
Bryonia 30C, HPUS | Relieves body aches
Gelsemium sempervirens 30C, HPUS | Relieves fever, chills and weakness
Nux vomica 30C, HPUS | Relieves sneezing and chills
Pulsatilla 30C, HPUS | Relieves chills due to fever

"HPUS" indicates that the ingredient is officially included in the Homeopathic Pharmacopeia of the United States and the manufacturer has followed all guidelines set forth.

Statement of Identity: Nasal decongestant; antiussive; analgesic/antipyretic.

Uses

For the relief of the symptoms of the flu, such as sinus congestion, runny nose, deep coughing, headache, body aches, chills and fever.

Warnings

- Do not use if outer package seal is broken.
- Stop use and consult a doctor if pain gets worse or lasts more than 10 days, fever gets worse or lasts more than 3 days, you have difficulty swallowing, redness or swelling is present in the painful area, or any new symptoms appear.
- Consult a doctor before use in children younger than 8 years of age.

PREGNANCY OR BREAST FEEDING

- If pregnant or breast-feeding, consult a health professional before use.

- Keep out of reach of children.

Directions

(adults and children 8 years of age and older)

Chew one tablet thoroughly, allowing it to dissolve in the mouth, then swallow. Repeat every 4 hours as needed.

Other information

- Safe to take with all other medications.
- Store at 68-77°F (20-25°C) and keep out of direct sunlight.
- Avoid humid or damp storage conditions. Close well when not in use.

Inactive Ingredients

Lactose, magnesium stearate (vegetable source), stevia leaf extract.

Questions? Call toll free or email us at:

1-888-60-B-WELL (1-888-602-9355)

info@homeostasislabs.com